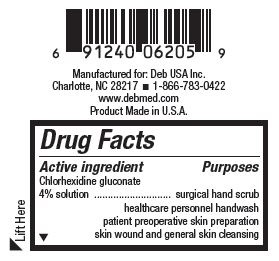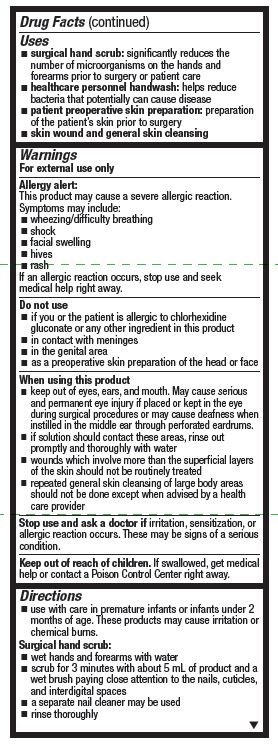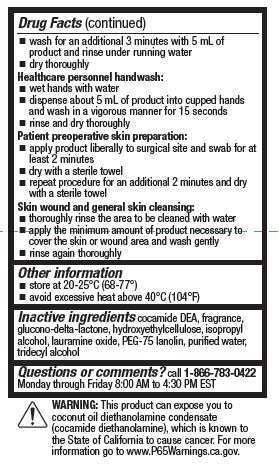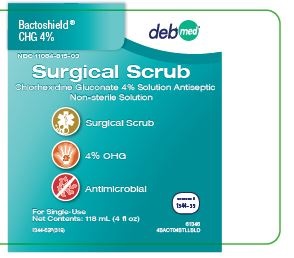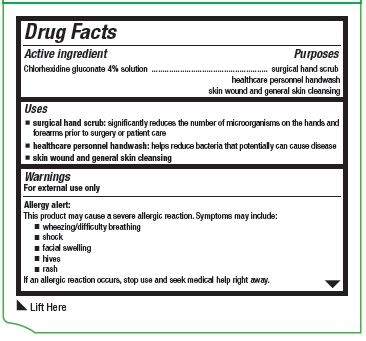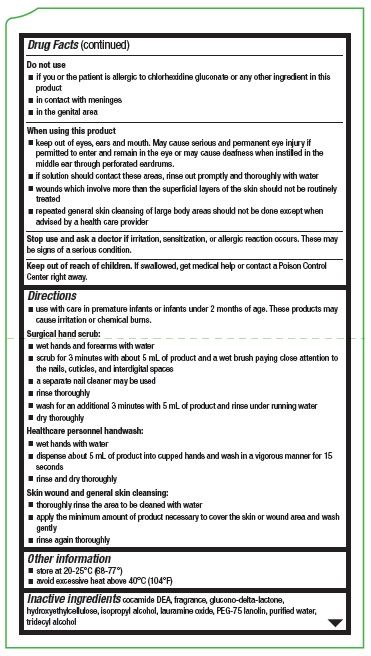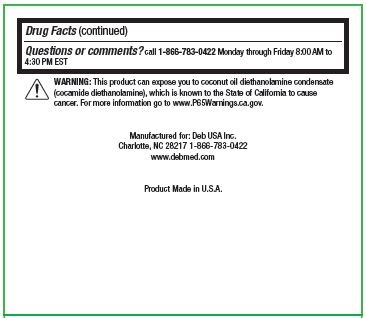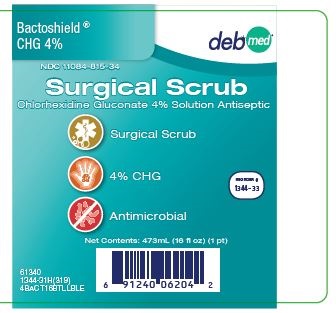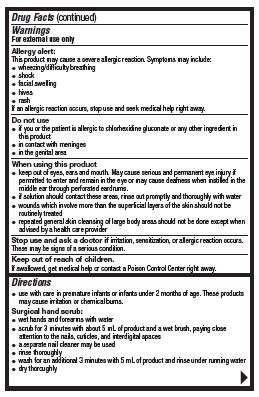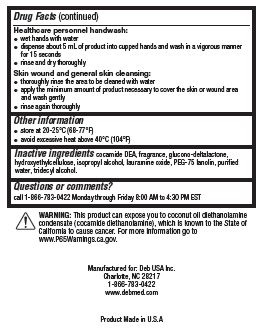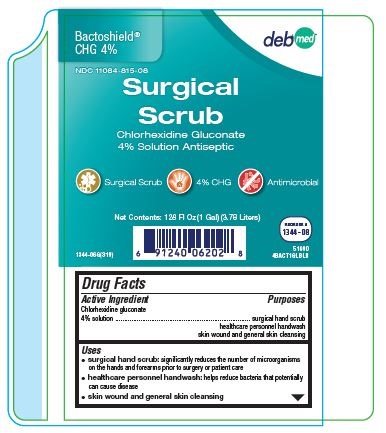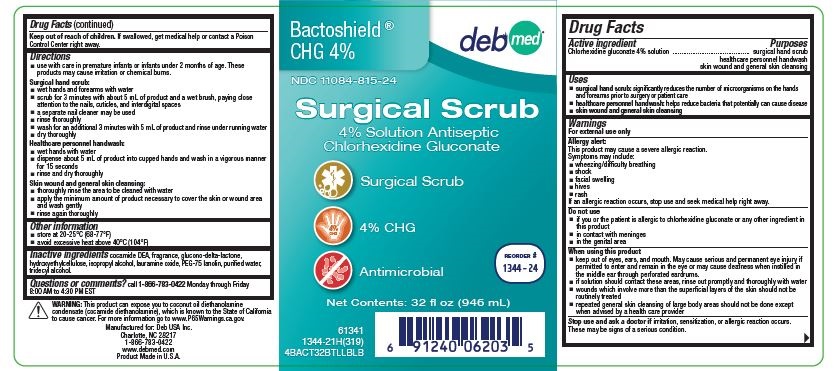 DRUG LABEL: Bactoshield CHG
NDC: 0116-1344 | Form: SOLUTION
Manufacturer: Xttrium Laboratories, Inc.
Category: otc | Type: HUMAN OTC DRUG LABEL
Date: 20191106

ACTIVE INGREDIENTS: CHLORHEXIDINE GLUCONATE 40 mg/1 mL
INACTIVE INGREDIENTS: COCO DIETHANOLAMIDE; GLUCONOLACTONE; HYDROXYETHYL CELLULOSE (5000 MPA.S AT 1%); ISOPROPYL ALCOHOL; LAURAMINE OXIDE; PEG-75 LANOLIN; WATER; TRIDECYL ALCOHOL

Bactoshield CHG® 4%
Chlorhexidine Gluconate Solution

Drug Facts

Active ingredient

chlorhexidine gluconate 4% solution

Purposes

surgical hand scrub
healthcare personnel handwash
patient preoperative skin preparation
skin wound and general skin cleansing

Uses

- surgical hand scrub: significantly reduces the number of microorganisms on the hands and forearms prior to surgery or patient care
- healthcare personnel handwash: helps reduce bacteria that potentially can cause disease
- patient preoperative skin preparation: preparation of the patient's skin prior to surgery
- skin wound and general skin cleansing

Warnings

For external use only

Allergy alert:

This product may cause a sever allergic reaction. Symptoms may include:

- wheezing/difficulty breathing
- shock
- facial swelling
- hives
- rash

If an allergic reaction occurs, stop use and seek medical help right away.

Do not use

- if you or the patient is allergic to chlorhexidine gluconate or any other ingredient in this product
- in contact with meninges
- in the genital area
- as a preoperative skin preparation of the head or face

When using this product

- keep out of eyes, ears, and mouth. May cause serious and permanent eye injury if placed or kept in the eye during surgical procedures or may cause deadness when instilled in the middle ear through perforated eardrums.
- if solution should contact these areas, rinse out prompty and thoroughly with water
- wounds which involve more than the superficial layers of the skin should not be routinely treated
- repeated general skin cleansing of large body areas should not be done except when advised by a health care provider

Stop use and ask a doctor if irritation, sensitization, or allergic reaction occurs. These may be signs of a serious condition.

Keep out of reach of children.

If swallowed, get medical help or contact a Poison Control Center right away.

Directions

- Use with care in premature infants or infants under 2 months of age. These products may cause irritation or chemical burns.

Surgical hand scrub:

- wet hands and forearms with water
- scrub for 3 minutes with about 5 ml of product and a wet brush, paying close attention to the nails, cuticles, and interdigital spaces
- a separate nail cleaner may be used
- rinse thoroughly
- wash for an additional 3 minutes with 5 ml of product and rinse under running water
- dry thoroughly

Healthcare personnel handwash:

- wet hands with water
- dispense about 5 ml of product into cupped hands and wash in a vigorous manner for 15 seconds
- rinse and dry thoroughly

Patient preoperative skin preparation:

- apply product liberally to surgical site and swab for at least 2 minutes
- dry with a sterile towel
- repeat procedure for an additional 2 minutes and dry with a sterile towel

Skin wound and general skin cleansing:

- thoroughly rinse the area to be cleaned with water
- apply the minimum amount of product necessary to cover the skin or wound area and wash gently
- rinse again thoroughly

Other information

- store at 20-25°C (68-77°F)
- void excessive heat above 40°C (104°F)

Inactive ingredients

cocamide DEA, fragrance, glucono-delta-lactone, hydroxyethylcellulose, isopropyl alcohol, lauramine oxide, PEG-75 lanolin, purified water, tridecyl alcohol

Questions or comments?

Call 1-800-548-4873 Monday through Friday 8:00 AM to 4:30 PM EST

OTHER SAFETY INFORMATION

WARNING: This product can expose you to coconut oil diethanolamine condensate (cocamide diethanolamine), which is known to the State of California to cause cancer. For more information go to www.P65Warnings.ca.gov.

PACKAGE LABEL

Bactoshield ® CHG 4%

NDC 11084-815-03

Surgical Scrub

Chlorhexidine Cluconate 4% Solution Antiseptic

Non-sterile Solution

Surgical Scrub

4% CHG

Antimicrobial

For Single-Use

Net Contents: 118 mL (4 fl oz)

REORDER #1344-39

1344-52F(319)

61346

4BACT04BTLLBLD

Bactoshield ® CHG 4%

NDC 11084-815-34

Surgical Scrub

Chlorhexidine Gluconate 4% Solution Antiseptic

Surgical Scrub

4% CHG

Antimicrobial

Net Contents: 473mL (16 fl oz) (1 pt)

REORDER #1344-33

61340

1344-31H(319)

4BACT16BTLLBLE

Bactoshield ® CHG 4%

NDC 11084-815-24

Surgical Scrub

4% Solution Antiseptic Chlorhexidine Gluconate

Surgical Scrub

4% CHG

Antimicrobial

Net Contents: 32 fl oz (946 mL)

REORDER #1344-24

61341

1344-21H(319)

4BACT32BTLLBLB

Bactoshield ® CHG 4%

NDC 11084-815-08

Surgical Scrub

Chlorhexidine Gluconate 4% Solution Antiseptic

Surgical Scrub

4% CHG

Antimicrobial

Net Contents: 128 fl oz (1 Gal) (3.78 Liters)

REORDER #1344-08

1344-06G(319)

51690

4BACT1GLBLB